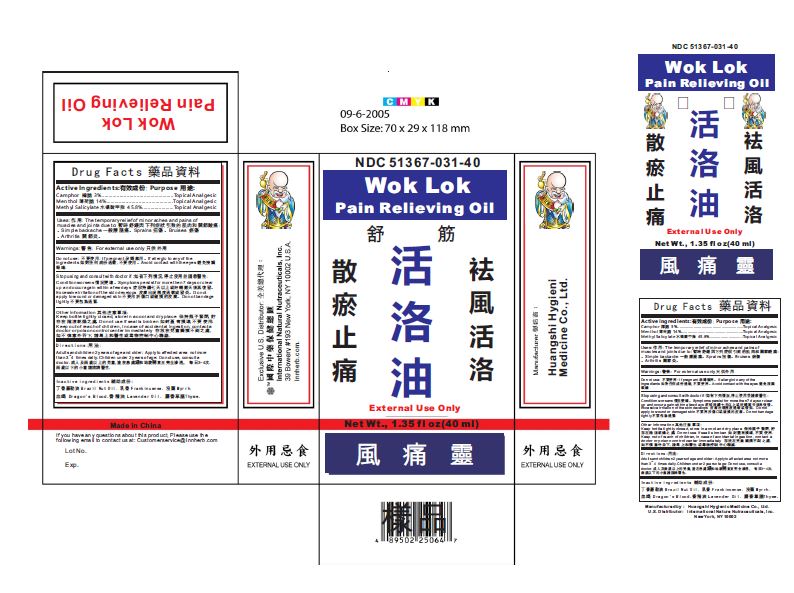 DRUG LABEL: Wok Lok Pain Relieving Oil
NDC: 51367-031 | Form: OIL
Manufacturer: International Nature Nutraceuticals Inc.
Category: otc | Type: HUMAN OTC DRUG LABEL
Date: 20170926

ACTIVE INGREDIENTS: CAMPHOR (NATURAL) 1.2 mg/1 1; MENTHOL 5.6 mg/1 1; METHYL SALICYLATE 18.32 mg/1 1
INACTIVE INGREDIENTS: BRAZIL NUT OIL; FRANKINCENSE; MYRRH; DRAGON'S BLOOD; LAVENDER OIL; THYME

Drug Facts

Active Ingredients

Camphor 樟脑 3%....................................................Topical Analgesic
Menthol 薄荷脑 14%................................................Topical Analgesic
Methyl Salicylate ⽔楊酸甲脂 45.8%.......................Topical Analgesic

Uses:

The temporary relief of minor aches and pains of
muscles and joints due to: 暫時舒緩因下列症狀引致的肌肉和關節酸痛:
。Simple backache 一般腰腿痛。Sprains 扭傷。Bruises 瘀傷
。Arthritis 關節炎。

Warnings

For external use only

Do Not Use

pregnant 孕婦禁用。If allergic to any of the
ingredients 如對任何成份過敏,不要使用。Avoid contact with the eyes 避免接觸
眼睛.

Stop using and consult with doctor if:

Condition worsens 情況變壞。Symptoms persist for more then 7 days or clear
up and occur again within a few days 症狀持續七天以上或好轉數天後再復發。
Excessive irritation of the skin develops 皮膚出現極度過敏或發炎。Do not
apply to wound or damaged skin 不要用於傷口或破損的皮膚。Do not bandage
tightly 不要包紮過緊.

Other Information

Keep bottle tightly closed, store in a cool and dry place 保持瓶子緊閉,貯
存在陰涼乾燥之處. Do not use if seal is broken 如封蓋有損壞,不要使用.

Keep out of reach of children

in case of accidental ingestion, contact a
doctor or poison control center immediately 存放在兒童觸摸不到之處,
如不慎意外吞下,請馬上和醫生或毒物控制中心聯絡.

Directions

Adults and children 2 years of age and older: Apply to affected area not more
than 3~ 4 times daily. Children under 2 years of age: Do not use, consult a
doctor. 成人及兩歲以上的兒童, 塗在患處緩和地旋轉直至完全滲透， 每日3- 4次.
兩歲以下的小童請諮詢醫生.

Inactive Ingredients

丁香羅勒油 B r a z i l N u t O i l . 乳香 F r a n k i n c e n s e . 沒藥 M y r r h . 血竭 D r a g o n ' s B l o o d .香精油 L a v e n d e r O i l . 麝香草腦T h y m e .